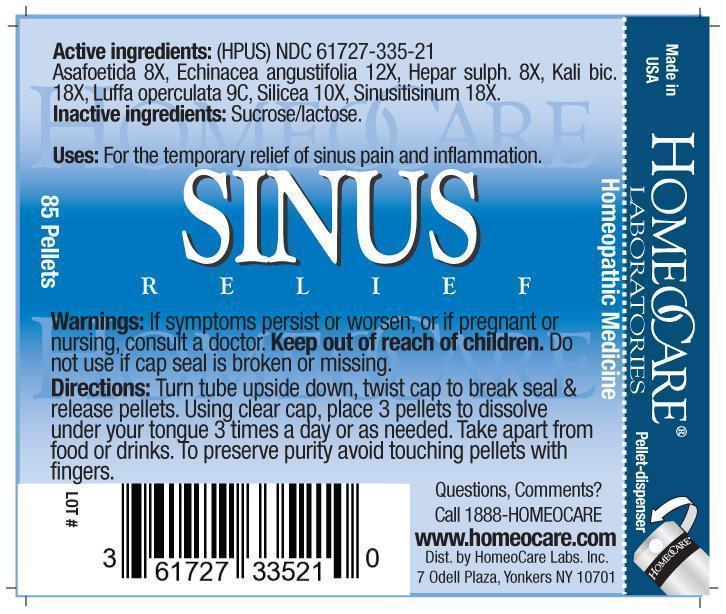 DRUG LABEL: Sinus Relief
NDC: 61727-335 | Form: PELLET
Manufacturer: Homeocare Laboratories
Category: homeopathic | Type: HUMAN OTC DRUG LABEL
Date: 20181231

ACTIVE INGREDIENTS: ASAFETIDA 8 [hp_X]/4 g; ECHINACEA ANGUSTIFOLIA 12 [hp_X]/4 g; CALCIUM SULFIDE 8 [hp_X]/4 g; POTASSIUM DICHROMATE 18 [hp_X]/4 g; LUFFA OPERCULATA WHOLE 9 [hp_C]/4 g; SILICON DIOXIDE 10 [hp_X]/4 g; SINUSITISINUM 18 [hp_X]/4 g
INACTIVE INGREDIENTS: SUCROSE; LACTOSE

Sinus Relief

Active ingredients:

Asafoetida 8X, Echinacea angustifolia 12X, Hepar sulph. 8X, Kali bic. 18X, Luffa operculata 9C, Silicea 10X, Sinusitisinum 18X.

Inactive ingredients:

Sucrose/lactose.

Purpose:

For the temporary relief of sinus pain and inflammation.

Warnings:

If symptoms persist or worsen, or if pregnant or nursing, consult a doctor. Keep out of reach of children. Do not use if cap seal is broken or missing.

Indications & Usage:

Turn tube upside down, twist cap to break seal & release pellets. Using clear cap, place 3 pellets to dissolve under your tongue 3 times a day or as needed. Take apart from food or drinks. To preserve purity avoid touching pellets with fingers.

Dosage & Administration:

Turn tube upside down, twist cap to break seal & release pellets. Using clear cap, place 3 pellets to dissolve under your tongue 3 times a day or as needed. Take apart from food or drinks. To preserve purity avoid touching pellets with fingers.

Keep out of reach of children.

Sinus Relief

Homeopathic Medicine

85 Pellets

SINUS-RELIEF.jpg